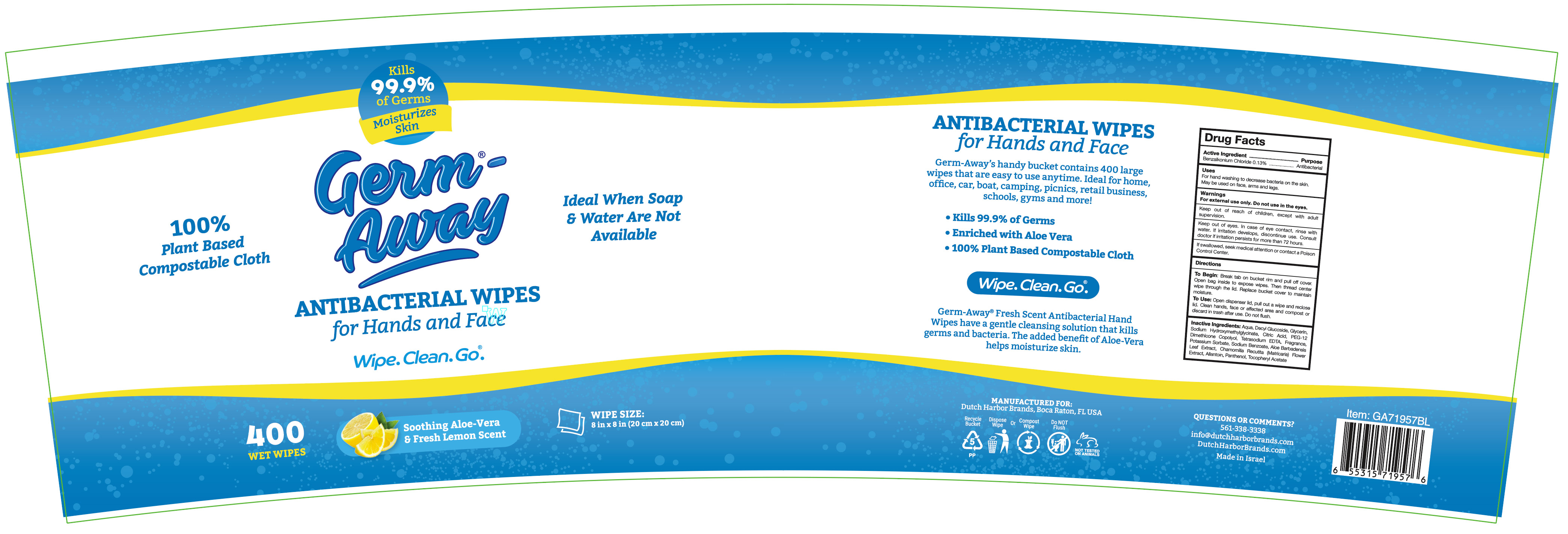 DRUG LABEL: Germ Away
NDC: 74680-101 | Form: CLOTH
Manufacturer: Unico International Trading Corp
Category: otc | Type: HUMAN OTC DRUG LABEL
Date: 20260108

ACTIVE INGREDIENTS: BENZALKONIUM CHLORIDE 1.3 mg/1 g
INACTIVE INGREDIENTS: ALPHA-TOCOPHEROL ACETATE; SODIUM HYDROXYMETHYLGLYCINATE; GLYCERIN; CHAMOMILE; ANHYDROUS CITRIC ACID; PANTHENOL; PEG-12 DIMETHICONE (300 CST); DECYL GLUCOSIDE; EDETATE SODIUM; WATER; ALOE VERA LEAF; POTASSIUM SORBATE; SODIUM BENZOATE; ALLANTOIN; 2,2'-OXYDIPROPANOL; COUMARIN; DIPHENYL ETHER; 3,7-DIMETHYL-1-OCTANOL; CP FORMATE; TETRAHYDROLINALOOL; EUCALYPTOL

Germ Away

Active Ingredient

Benzalkonium Chloride 0.1%

Keep out of the reach of children.

Keep out of reach of children, except with adult supervision.

Warnings

For external use only. Do not use in the eyes.

Keep out of eyes. In case of eye contact, rinse with water. If irritation develops, discontinue use. Consult doctor if irritation persists for more than 72 hours.

If swallowed, seek medical attention or contact a Poison Control Center.

Use

For use: gently pull wipe from the dispenser feed at an angle and in a downward motion. wet hands or surface thoroughly with the product and let dry, discard wipe in trash

Inactive Ingredients

Aqua, Decyl Glucoside, Glycerin, Sodium Hydroxymethylglycinate, Citric Acid, PEG-12 Dimethicone Copolyol, Tetrasodium EDTA, Potassium Sorbate, Sodium Benzoate, Aloe Barbadensis Leaf Extract, Chamomilla Recutita (Matricaria) Flower Extract, Allantoin, Panthenol, Tocopheryl Acetate

Purpose

Anti-bacterial

To dispense

Break tab on bucket rim and pull off cover. Open bag inside to expose wipes. Then thread center wipe through the lid. Replace bucket cover to maintain moisture.

To use

Pull one sheet from pack. Sanitize hands or other affected area. Discard in trash after use. Do not flush. Close tab after use to retain moisture.